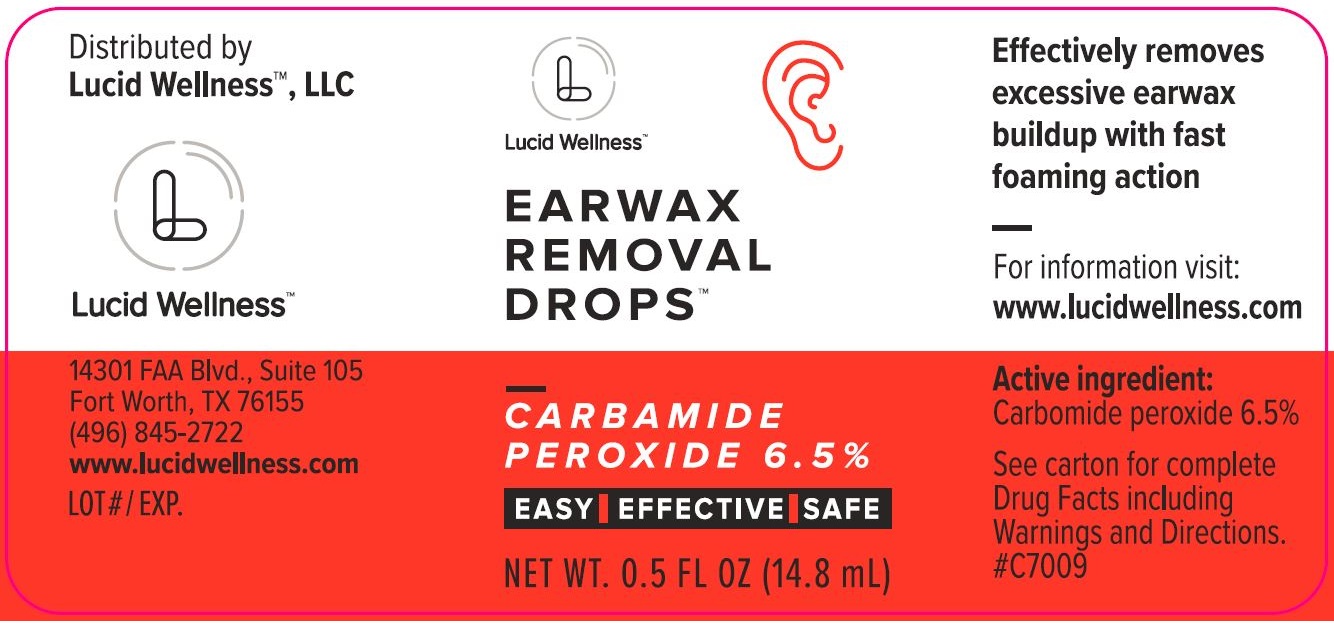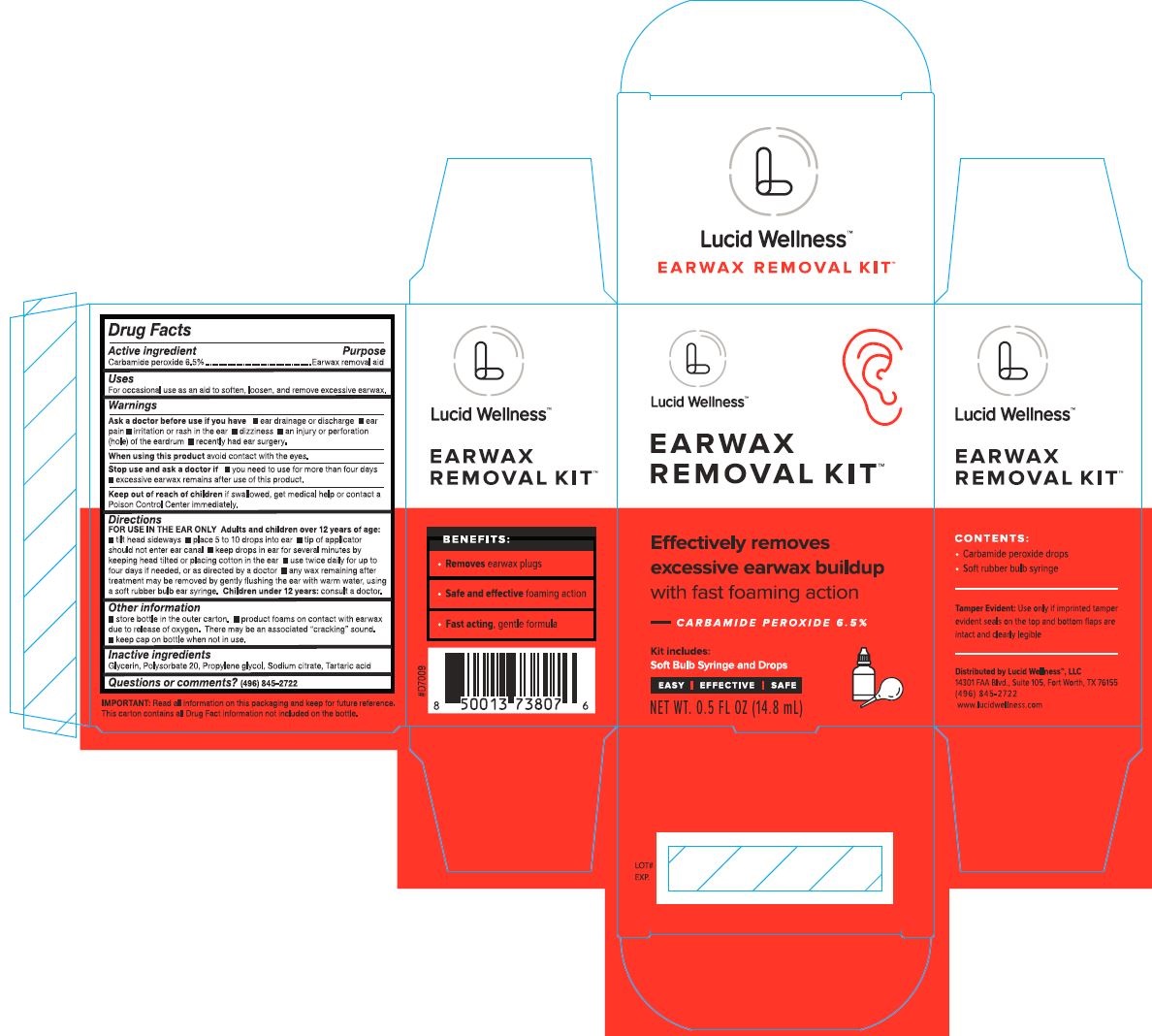 DRUG LABEL: Earwax Removal Kit
NDC: 76928-1000 | Form: LIQUID
Manufacturer: Lucid Wellness
Category: otc | Type: HUMAN OTC DRUG LABEL
Date: 20220113

ACTIVE INGREDIENTS: CARBAMIDE PEROXIDE 65 g/1 mL
INACTIVE INGREDIENTS: TARTARIC ACID; GLYCERIN; PROPYLENE GLYCOL; SODIUM CITRATE; POLYSORBATE 20

Lucid Wellness™ Earwax Removal Kit™

PURPOSE

Earwax removal aid

Drug Facts

Active ingredient

Active ingredient | Purpose
Carbamide peroxide 6.5% | Earwax removal aid

Uses

For occasional use as an aid to soften, loosen, and remove excessive earwax.

Warnings

Ask a doctor before use if you have ■ ear drainage or discharge ■ ear pain ■ irritation or rash in the ear ■ dizziness ■ an injury or per1oration (hole) of the eardrum ■ recently had ear surgery.

When using this product avoid contact with the eyes.

Stop use and ask a doctor if ■ you need to use for more than four days ■ excessive earwax remains after use of this product.

Keep out of reach of children if swallowed, get medical help or contact a Poison Control Center immediately.

Directions

FOR USE IN THE EAR ONLY Adults and children over 12 years of age: ■ tilt head sideways ■ place 5 to 10 drops into ear ■ tip of applicator should not enter ear canal ■ keep drops in ear for several minutes by keeping head tilted or placing cotton in the ear ■ use twice daily for up to four days if needed, or as directed by a doctor ■ any wax remaining after treatment may be removed by gently flushing the ear with warm water, using a soft rubber bulb ear syringe. Children under 12 years: consult a doctor.

Other information

■ store bottle in the outer carton. ■ product foams on contact with earwax due to release of oxygen. There may be an associated "cracking" sound. ■ keep cap on bottle when not in use.

Inactive ingredients

Glycerin, Polysorbate 20, Propylene glycol, Sodium citrate, Tartaric acid

Questions or comments?

(496) 845-2722

Principal Display Panel

Lucid Wellness™

EARWAX

REMOVAL KIT™

Effectively removes

excessive buildup

with fast foaming acion

— CARBAMIDE PEROXIDE 6.5%

Kit includes:

Soft BulbSyringe and Drops

EASY | EFFECTIVE | SAFE

NET WT. 0.5 FL OZ (14.8 mL)